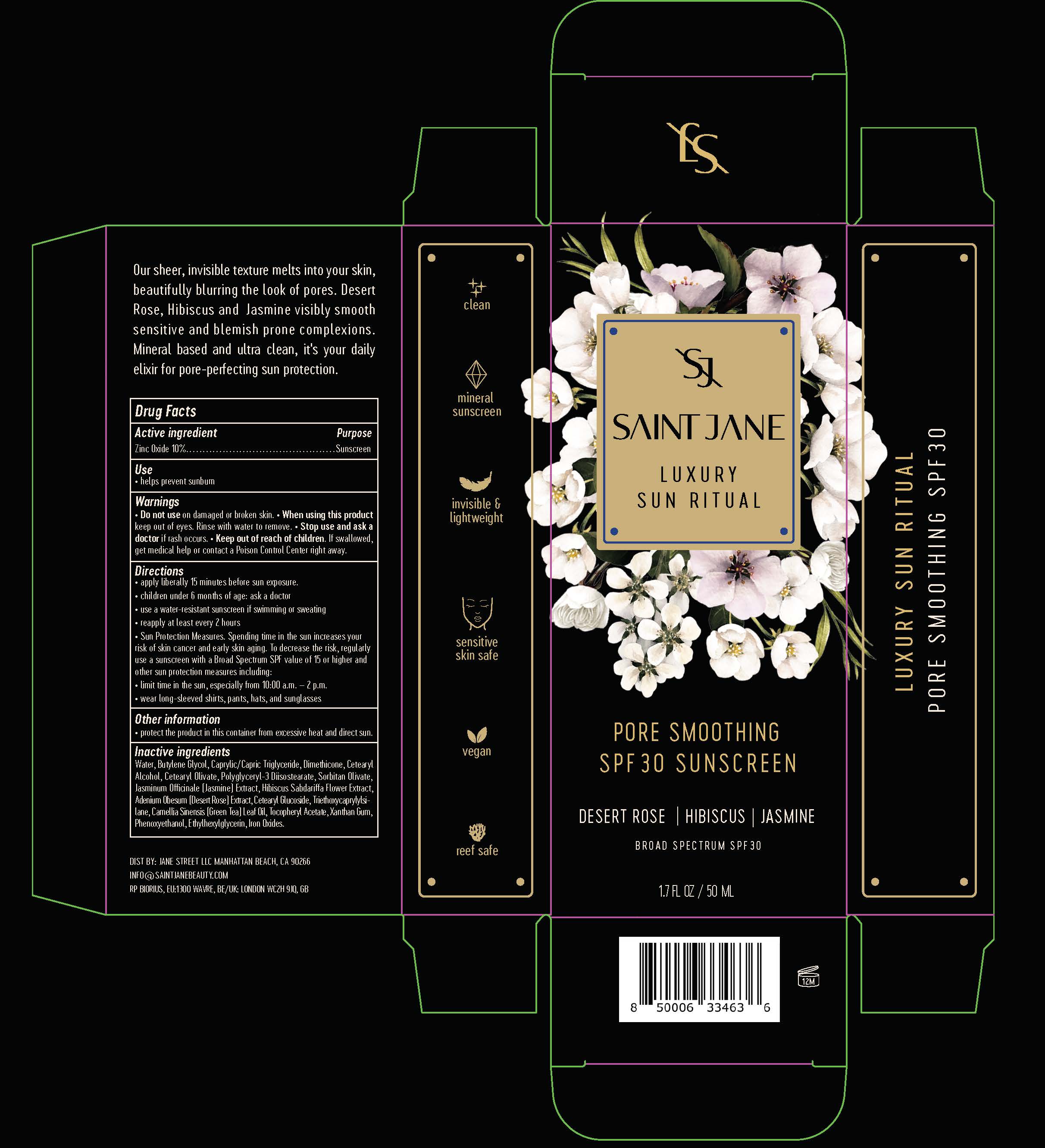 DRUG LABEL: LUXURY SUN RITUAL
NDC: 82404-101 | Form: LOTION
Manufacturer: JANE STREET LLC
Category: otc | Type: HUMAN OTC DRUG LABEL
Date: 20260107

ACTIVE INGREDIENTS: ZINC OXIDE 10 g/100 mL
INACTIVE INGREDIENTS: HIBISCUS SABDARIFFA FLOWER; SORBITAN OLIVATE; FERRIC OXIDE YELLOW; BUTYLENE GLYCOL; FERROSOFERRIC OXIDE; ETHYLHEXYLGLYCERIN; WATER; MEDIUM-CHAIN TRIGLYCERIDES; DIMETHICONE; CETOSTEARYL ALCOHOL; .ALPHA.-TOCOPHEROL ACETATE; CETEARYL OLIVATE; POLYGLYCERYL-3 DIISOSTEARATE; CETEARYL GLUCOSIDE; PHENOXYETHANOL; XANTHAN GUM; FERRIC OXIDE RED; GREEN TEA LEAF; TRIETHOXYCAPRYLYLSILANE; JASMINUM OFFICINALE FLOWER; ADENIUM OBESUM WHOLE

SJ (as PLD) - LUXURY SUN RITUAL (82404-101)

ACTIVE INGREDIENT

ZINC OXIDE 10%

PURPOSE

SUNSCREEN

USE

HELPS PREVENT SUNBURN

WARNINGS

- FOR EXTERNAL USE ONLY.

- DO NOT USE ON DAMAGED OR BROKEN SKIN.

WHEN USING THIS PRODUCT KEEP OUT OF EYES. RINSE WITH WATER TO REMOVE.

- STOP USE AND ASK A DOCTOR IF RASH OCCURS.

- KEEP OUT OF REACH OF CHILDREN. IF SWALLOWED, GET MEDICAL HELP OR CONTACT A POISON CONTROL CENTER RIGHT AWAY.

DIRECTIONS

- APPLY LIBERALLY 15 MINUTES BEFORE SUN EXPOSURE.
- CHILDREN UNDER 6 MONTHS OF AGE: ASK A DOCTOR.
- USE A WATER-RESISTANT SUNSCREEN IF SWIMMING OR SWEATING.
- REAPPLY AT LEAST EVERY 2 HOURS.
- SUN PROTECTION MEASURES: SPENDING TIME IN THE SUN INCREASES YOUR RISK OF SKIN CANCER AND EARLY SKIN AGING. TO DECREASE THIS RISK, REGULARLY USE A SUNSCREEN WITH A BROAD SPECTRUM SPF VALUE OF 15 OR HIGHER AND OTHER SUN PROTECTION MEASURES INCLUDING:
- LIMIT TIME IN THE SUN, ESPECIALLY FROM 10 A.M. - 2 P.M.
- WEAR LONG-SLEEVED SHIRTS, PANTS, HATS, AND SUNGLASSES.

OTHER INFORMATION

- PROTECT THE PRODUCT IN THIS CONTAINER FROM EXCESSIVE HEAT AND DIRECT SUN.

INACTIVE INGREDIENTS

Water, Butylene Glycol, Caprylic/Capric Triglyceride, Dimethicone, Cetearyl Alcohol, Cetearyl Olivate, Polyglyceryl-3 Diisostearate, Sorbitan Olivate, Jasminum Officinale (Jasmine) Extract, Hibiscus Sabdariffa Flower Extract, Adenium Obesum (Desert Rose) Extract, Cetearyl Glucoside, Triethoxycaprylylsilane, Camellia Sinensis (Green Tea) Leaf Oil, Tocopheryl Acetate, Xanthan Gum, Phenoxyethanol, Ethylhexylglycerin, Iron Oxides.